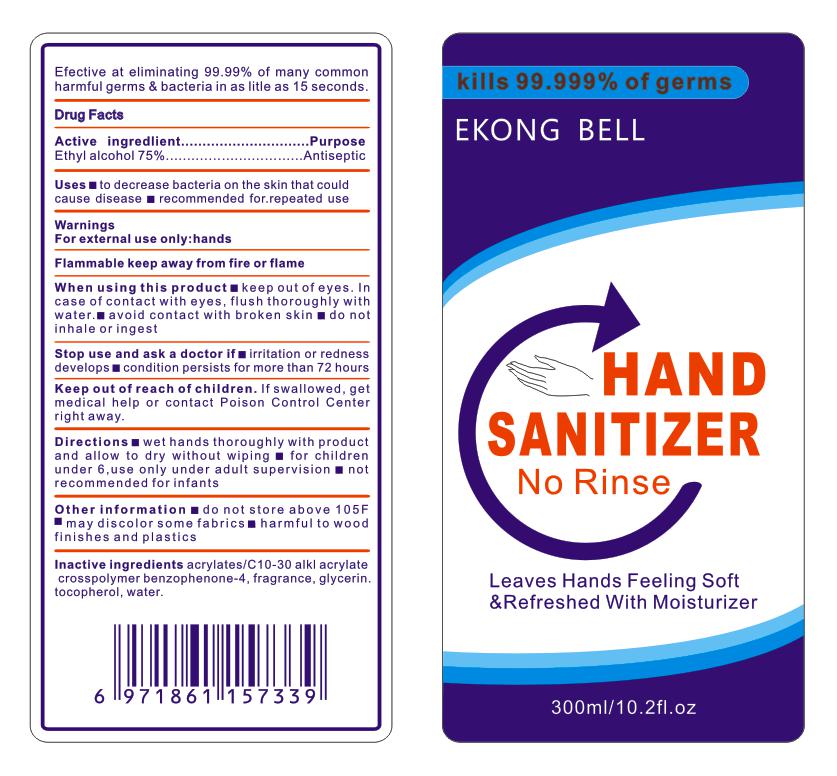 DRUG LABEL: Hand sanitizer
NDC: 55453-003 | Form: LIQUID
Manufacturer: Guangzhou Yikang Biotechnology Co., Ltd.
Category: otc | Type: HUMAN OTC DRUG LABEL
Date: 20200406

ACTIVE INGREDIENTS: ALCOHOL 210 mL/300 mL
INACTIVE INGREDIENTS: WATER; CARBOMER INTERPOLYMER TYPE A (55000 CPS); AMINOMETHYLPROPANOL; GLYCERIN

keep out of reach of children

ACTIVE INGREDIENT

Ethyl alcoho

INACTIVE INGREDIENT

water、ACRYLATES/C10-30 ALKYL ACRYLATE CROSSPOLYMER、AMINOMETHYL PROPANOL

PURPOSE

Disinfection

Sterilization
No Rinseing

INDICATIONS AND USAGE

Uses to decrease bacteria on the skin that could cause disease recommended for repeated use.

When using this product keep out of eyes. In case of contact with eyes, flush thoroughly with water. avoid contact with broken skin do not inhale oringest

WARNINGS

For external use only:hands

Stop use and ask a doctor if irritation or redness develops condition persists for more than 72 hours

DOSAGE AND ADMINISTRATION

Flammable keep away from fire or flame.